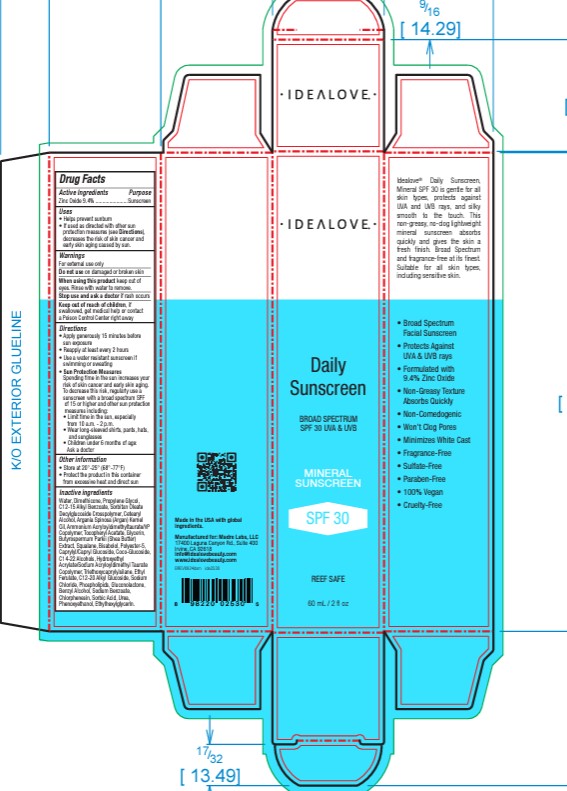 DRUG LABEL: Daily Sunscreen Broad Spectrum SPF 30 UVA UVB
NDC: 82287-0001 | Form: LOTION
Manufacturer: IHerb, LLC
Category: otc | Type: HUMAN OTC DRUG LABEL
Date: 20250114

ACTIVE INGREDIENTS: ZINC OXIDE 9.4 mg/100 mL
INACTIVE INGREDIENTS: CETEARYL ALCOHOL; ARGANIA SPINOSA KERNEL OIL; AMMONIUM ACRYLOYLDIMETHYLTAURATE/VP COPOLYMER; SORBIC ACID; SHEANUT; SQUALENE; SODIUM CHLORIDE; GLYCERIN; SODIUM BENZOATE; UREA; COCO-GLUCOSIDE; C14-22 ALCOHOLS; ETHYL FERULATE; GLUCONOLACTONE; WATER; PROPYLENE GLYCOL; C12-20 ALKYL GLUCOSIDE; POLYESTER-5 (TG-38); CAPRYLYL/CAPRYL GLUCOSIDE; ALPHA-TOCOPHEROL ACETATE; BENZYL ALCOHOL; OMEGA-3 FATTY ACIDS; CHLORPHENESIN; C12-15 ALKYL BENZOATE; SORBITAN OLEATE DECYLGLUCOSIDE CROSSPOLYMER; ETHYLHEXYLGLYCERIN; BISABOLOL; HYDROXYETHYL ACRYLATE/SODIUM ACRYLOYLDIMETHYL TAURATE COPOLYMER (45000 MPA.S AT 1%); TRIETHOXYCAPRYLYLSILANE; PHENOXYETHANOL

HEALTH CLAIM

Idealove® Daily Sunscreen,
Mineral SPF 30 is gentle for all
skin types, protects against
UVA and UVB rays, and silky
smooth to the touch. This
non-greasy, no-clog lightweight
mineral sunscreen absorbs
quickly and gives the skin a
fresh finish. Broad Spectrum
and fragrance-free at its finest.
Suitable for all skin types,
including sensitive skin.

• Broad Spectrum
Facial Sunscreen
• Protects Against
UVA & UVB rays
• Formulated with
9.4% Zinc Oxide
• Non-Greasy Texture
Absorbs Quickly
• Non-Comedogenic
• Won’t Clog Pores
• Minimizes White Cast
• Fragrance-Free
• Sulfate-Free
• Paraben-Free
• 100% Vegan
• Cruelty-Free

PATIENT COUNSELING INFORMATION

Made in the USA with global
ingredients.

Manufactured for: Madre Labs, LLC
17400 Laguna Canyon Rd., Suite 400
Irvine, CA 92618

info@idealovebeauty.com
www.idealovebeauty.com
BREV0924dsm ide2530

8 98220 02530 5

see

QR Code.jpeg.jpg

see

UPC.jpg.jpg

Drug Facts
Active Ingredients Purpose
Zinc Oxide 9.4% .......................Sunscreen

Warnings
For external use only

Do not use on damaged or broken skin

When using this product keep out of
eyes. Rinse with water to remove.

Stop use and ask a doctor if rash occurs

Keep out of reach of children, if
swallowed, get medical help or contact
a Poison Control Center right away

PATIENT COUNSELING INFORMATION

• Sun Protection Measures
Spending time in the sun increases your
risk of skin cancer and early skin aging.
To decrease this risk, regularly use a
sunscreen with a broad spectrum SPF
of 15 or higher and other sun protection
measures including:
• Limit time in the sun, especially
from 10 a.m. - 2 p.m.
• Wear long-sleeved shirts, pants, hats,
and sunglasses
• Children under 6 months of age:
Ask a doctor

Other information
• Store at 20°-25° (68°-77°F)
• Protect the product in this container
from excessive heat and direct sun

Inactive ingredients
Water, Dimethicone, Propylene Glycol,
C12-15 Alkyl Benzoate, Sorbitan Oleate
Decylglucoside Crosspolymer, Cetearyl
Alcohol, Argania Spinosa (Argan) Kernel
Oil, Ammonium Acryloyldimethyltaurate/VP
Copolymer, Tocopheryl Acetate, Glycerin,
Butyrospermum Parkii (Shea Butter)
Extract, Squalane, Bisabolol, Polyester-5,
Caprylyl/Capryl Glucoside, Coco-Glucoside,
C14-22 Alcohols, Hydroxyethyl
Acrylate/Sodium Acryloyldimethyl Taurate
Copolymer, Triethoxycaprylylsilane, Ethyl
Ferulate, C12-20 Alkyl Glucoside, Sodium
Chloride, Phospholipids, Gluconolactone,
Benzyl Alcohol, Sodium Benzoate,
Chlorphenesin, Sorbic Acid, Urea,
Phenoxyethanol, Ethylhexylglycerin.

STATEMENT OF IDENTITY

mineral sunscreen

Directions
• Apply generously 15 minutes before
sun exposure
• Reapply at least every 2 hours
• Use a water resistant sunscreen if
swimming or sweating

INDICATIONS AND USAGE

Uses • Helps prevent sunburn • If used as directed with other sun protection measures (see Directions), decreases the risk of skin cancer and early skin aging caused by sun.

PACKAGE LABEL

• IDEΛLOVE •

Daily Sunscreen

BROAD SPECTRUM
SPF 30 UVA & UVB

MINERAL SUNSCREEN

SPF 30
REEF SAFE

60 mL / 2 fl oz